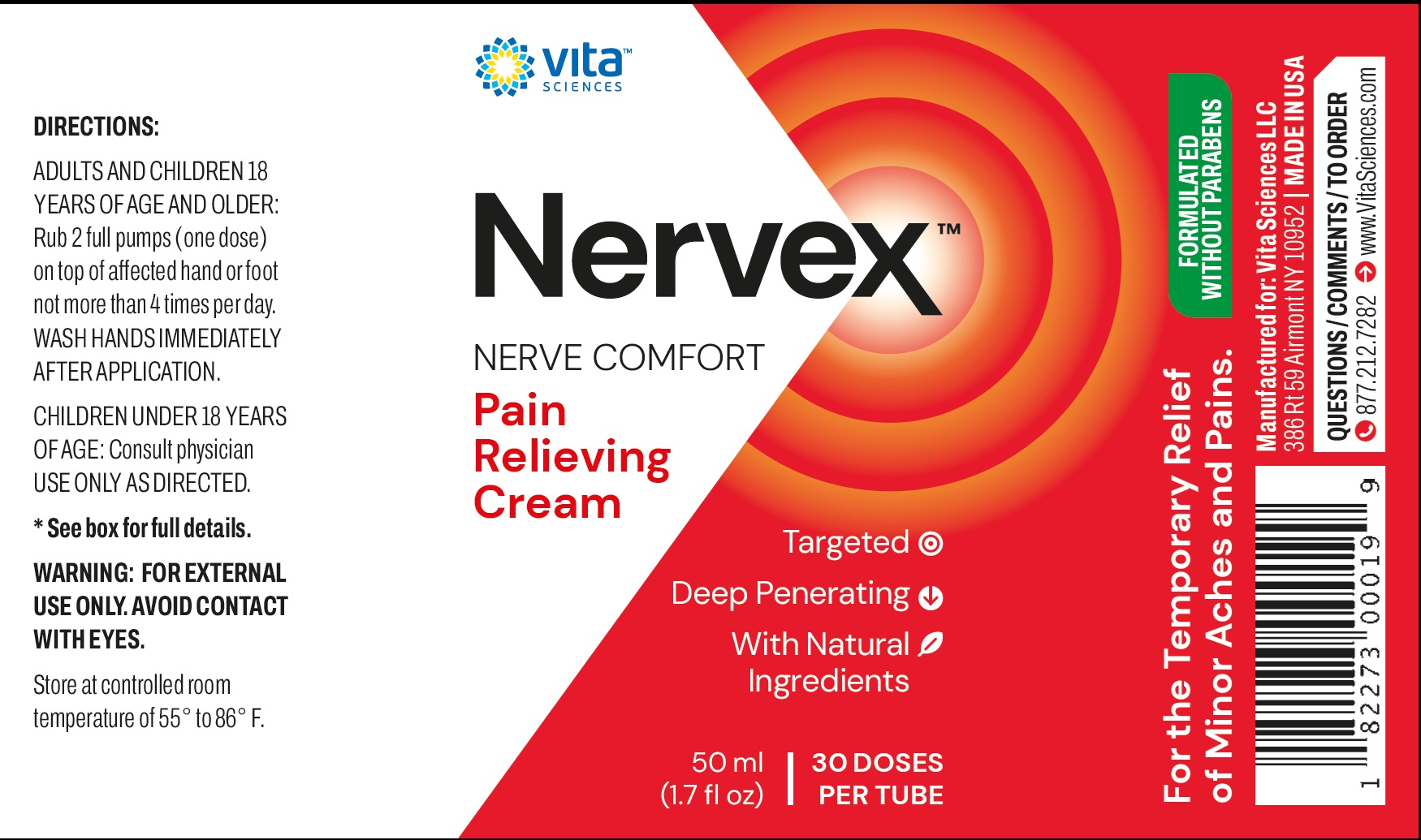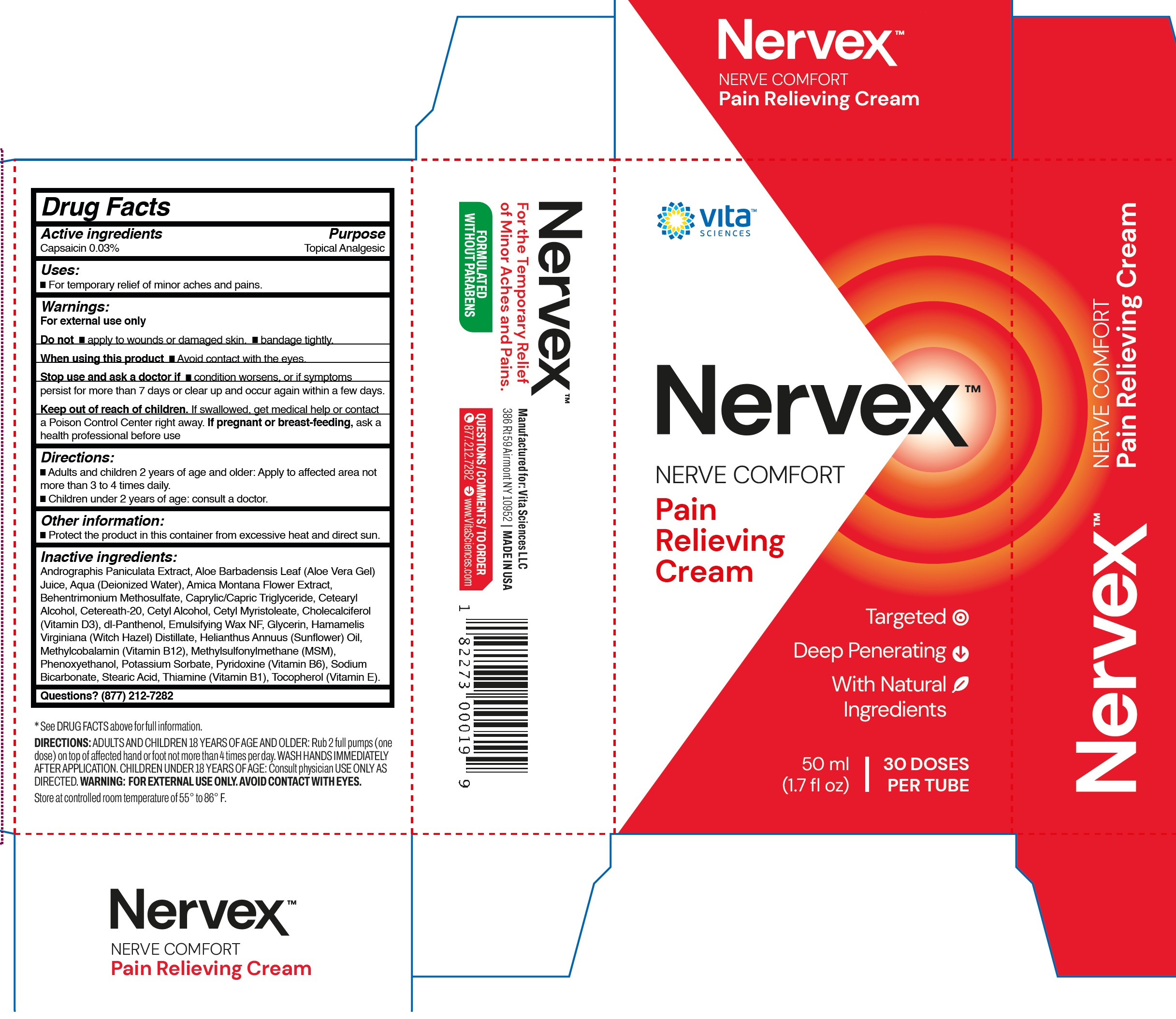 DRUG LABEL: Nervex Pain Relieving
NDC: 84834-542 | Form: CREAM
Manufacturer: VITA SCIENCES, LLC
Category: otc | Type: HUMAN OTC DRUG LABEL
Date: 20241014

ACTIVE INGREDIENTS: CAPSAICIN 0.3 mg/1 mL
INACTIVE INGREDIENTS: ANDROGRAPHIS PANICULATA WHOLE; ALOE VERA LEAF; WATER; BEHENTRIMONIUM METHOSULFATE; MEDIUM-CHAIN TRIGLYCERIDES; CETOSTEARYL ALCOHOL; POLYOXYL 20 CETOSTEARYL ETHER; CETYL ALCOHOL; CETYL MYRISTOLEATE; CHOLECALCIFEROL; PANTHENOL; GLYCERIN; WITCH HAZEL; HELIANTHUS ANNUUS FLOWERING TOP; CYANOCOBALAMIN; DIMETHYL SULFONE; PHENOXYETHANOL; POTASSIUM SORBATE; PYRIDOXINE; SODIUM BICARBONATE; STEARIC ACID; THIAMINE; TOCOPHEROL

Nervex Pain Relieving Cream

Active ingredients

Capsaicin 0.03%

Purpose

Topical Analgesic

Uses:

- For temporary relief of minor aches and pains.

Warnings:

For external use only

Do not

- apply to wounds or damaged skin.
- bandage tightly.

When using this product

- Avoid contact with the eyes.

Stop use and ask a doctor if

- condition worsens, or if symptoms persist for more than 7 days or clear up and occur again within a few days.

Keep out of reach of children.

If swallowed, get medical help or contact a Poison Control Center right away.

If pregnant or breast-feeding,

ask a health professional before use

Directions:

- Adults and children 2 years of age and older: Apply to affected area not more than 3 to 4 times daily.
- Children under 2 years of age: consult a doctor.

Other information:

- Protect the product in this container from excessive heat and direct sun.

Inactive ingredients:

Andrographis Paniculata Extract, Aloe Barbadensis Leaf (Aloe Vera Gel) Juice, Aqua (Deionized Water), Amica Montana Flower Extract, Behentrimonium Methosulfate, Caprylic/Capric Triglyceride, Cetearyl Alcohol, Cetereath-20, Cetyl Alcohol, Cetyl Myristoleate, Cholecalciferol (Vitamin D3), dl-Panthenol, Emulsifying Wax NF, Glycerin, Hamamelis Virginiana (Witch Hazel) Distillate, Helianthus Annuus (Sunflower) Oil, Methylcobalamin (Vitamin B12), Methylsulfonylmethane (MSM), Phenoxyethanol, Potassium Sorbate, Pyridoxine (Vitamin B6), Sodium Bicarbonate, Stearic Acid, Thiamine (Vitamin B1), Tocopherol (Vitamin E).

Questions?

(877) 212-7282